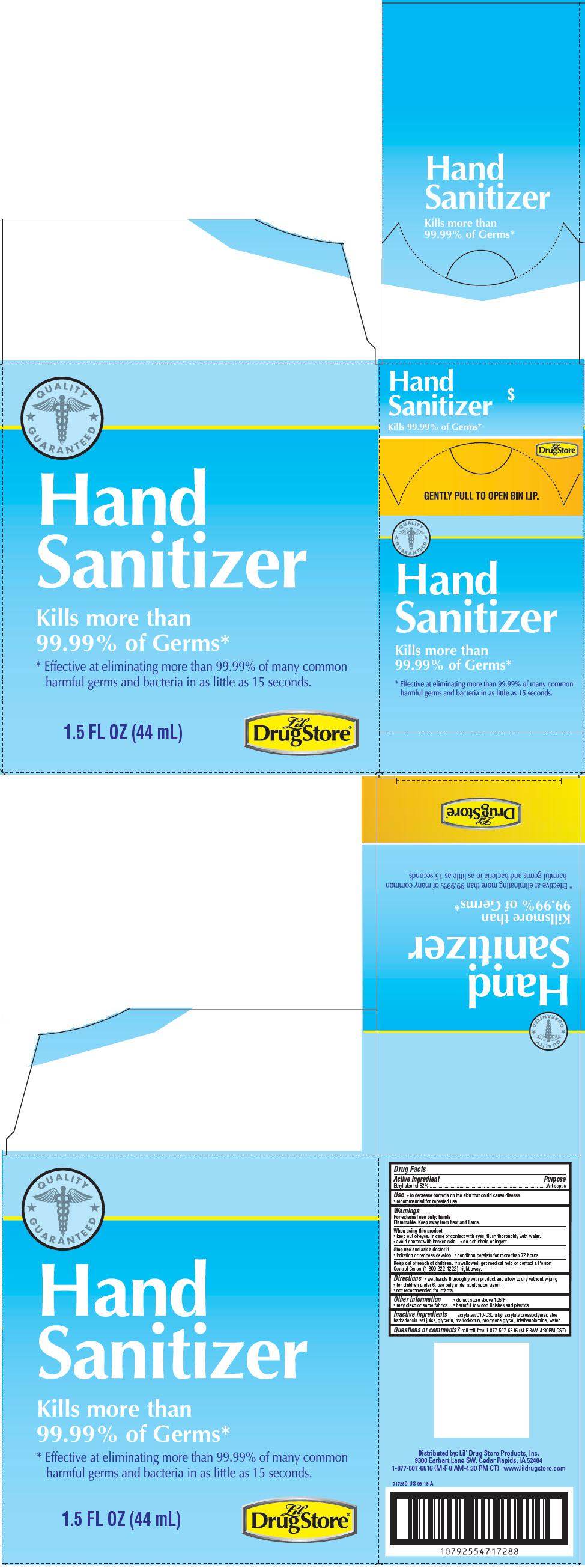 DRUG LABEL: Hand Sanitizer
NDC: 66715-7172 | Form: GEL
Manufacturer: Lil' Drug Store Products, Inc.
Category: otc | Type: HUMAN OTC DRUG LABEL
Date: 20241231

ACTIVE INGREDIENTS: ALCOHOL 62 mg/100 mL
INACTIVE INGREDIENTS: CARBOMER COPOLYMER TYPE A (ALLYL PENTAERYTHRITOL CROSSLINKED); ALOE VERA LEAF; GLYCERIN; MALTODEXTRIN; PROPYLENE GLYCOL; TROLAMINE; WATER

Hand Sanitizer, 1.5oz

Drug Facts

Active ingredient

Ethyl alcohol 62%

Purpose

Antiseptic

Use

- to decrease bacteria on the skin that could cause disease
- recommended for repeated use

Warnings

For external use only: hands

Flammable. Keep away from heat and flame.

When using this product

- keep out of eyes. In case of contact with eyes, flush thoroughly with water.
- avoid contact with broken skin
- do not inhale or ingest

Stop use and ask a doctor if

- irritation or redness develop
- condition persists for more than 72 hours

Keep out of reach of children. If swallowed, get medical help or contact a Poison Control Center (1-800-222-1222) right away.

Directions

- wet hands thoroughly with product and allow to dry without wiping
- for children under 6, use only under adult supervision
- not recommended for infants

Other information

- do not store above 105°F
- may discolor some fabrics
- harmful to wood finishes and plastics

Inactive ingredients

acrylates/C10-C30 alkyl acrylate crosspolymer, aloe barbadensis leaf juice, glycerin, maltodextrin, propylene glycol, triethanolamine, water

Questions or comments?

call toll-free 1-877-507-6516 (M-F 8AM-4:30PM CST)

Distributed by: Lil' Drug Store Products, Inc.
9300 Earhart Lane SW, Cedar Rapids, IA 52404

PRINCIPAL DISPLAY PANEL - 44 mL Bottle Carton

QUALITY
⋆ GUARANTEED ⋆

Hand
Sanitizer

Kills more than
99.99% of Germs*

* Effective at eliminating more than 99.99% of many common
harmful germs and bacteria in as little as 15 seconds.

1.5 FL OZ (44 mL)

Lil'
Drug Store®